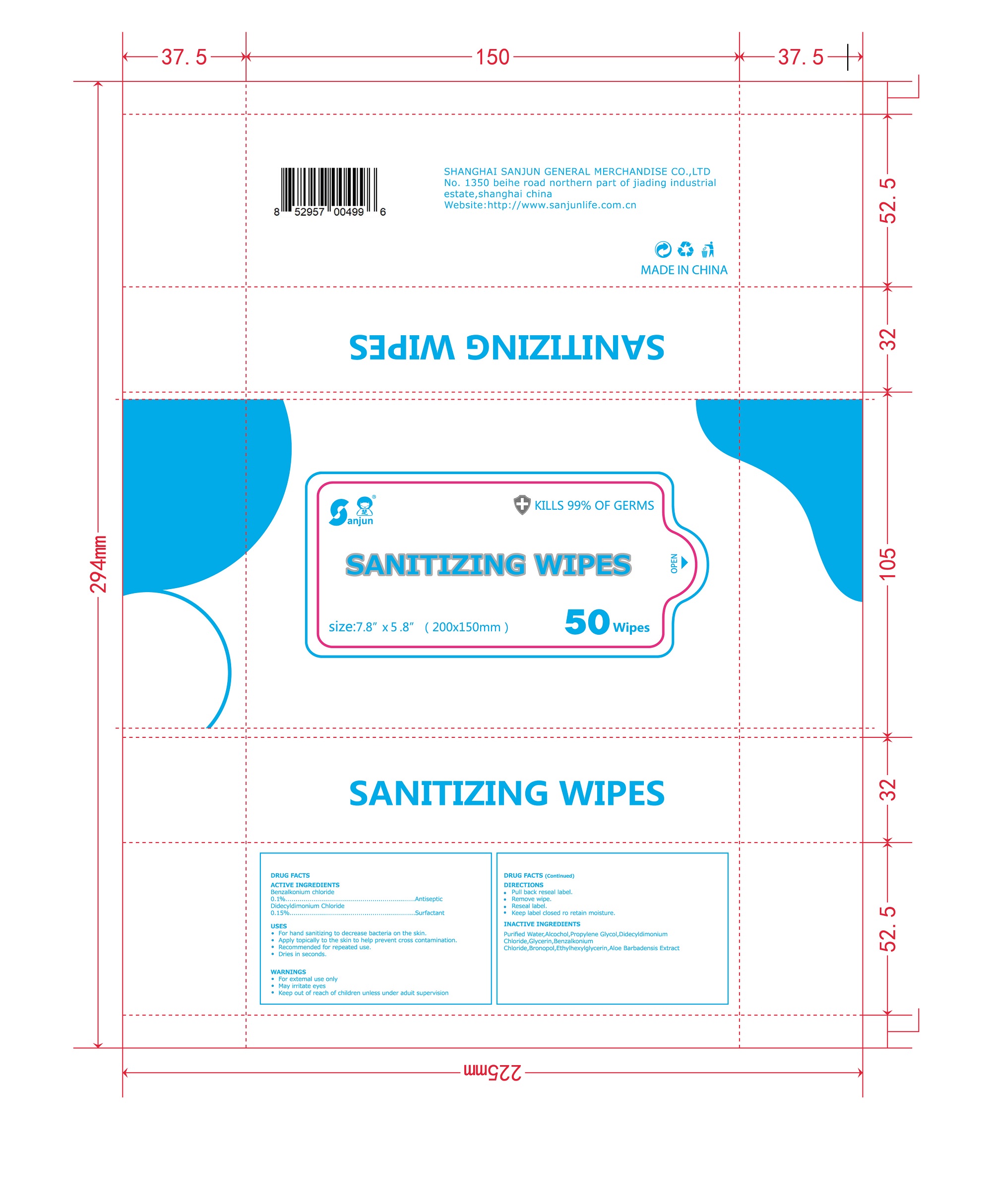 DRUG LABEL: SANITIZING WIPES
NDC: 75670-003 | Form: CLOTH
Manufacturer: SHANGHAI SANJUN GENERAL MERCHANDISE CO., LTD.
Category: otc | Type: HUMAN OTC DRUG LABEL
Date: 20220224

ACTIVE INGREDIENTS: BENZALKONIUM CHLORIDE 0.1 g/100 g; DIDECYLDIMONIUM CHLORIDE 0.15 g/100 g
INACTIVE INGREDIENTS: ALCOHOL; WATER; BRONOPOL; ETHYLHEXYLGLYCERIN; PROPYLENE GLYCOL; GLYCERIN; ALOE VERA FLOWER

75670-003 sanitizing wipes 0.1%Benzalkonium Chloride 0.15% Didecyldimonium Chloride

Active Ingredient

Benzalkonium Chloride 0. 1 %
Didecyldimonium Chloride 0.1 5%

PURPOSE

Antiseptic

Surfactant

USE

●For hand sanitizing to decrease bacteria on the skin.
●Apply topically to the skin to help prevent cross contamination.
●Recommended for repeated use.
Dries in seconds.

Warning

●For extemal use only
●May iritate eyes

Keep out of reach of children unless under
adult supervision

Directions

●Pull back reseal label.
●Remove wipe.
。Reseal label.
●Keep label closed ro retain moisture.

Inactive ingredients

Purified Water, Alcochol,Propylene Glycol,Didecyldimonium
Chloride,Glycerin, Benzalkonium
Chloride,Bronopol,Ethylhexylglycerin,Aloe Barbadensis Extract